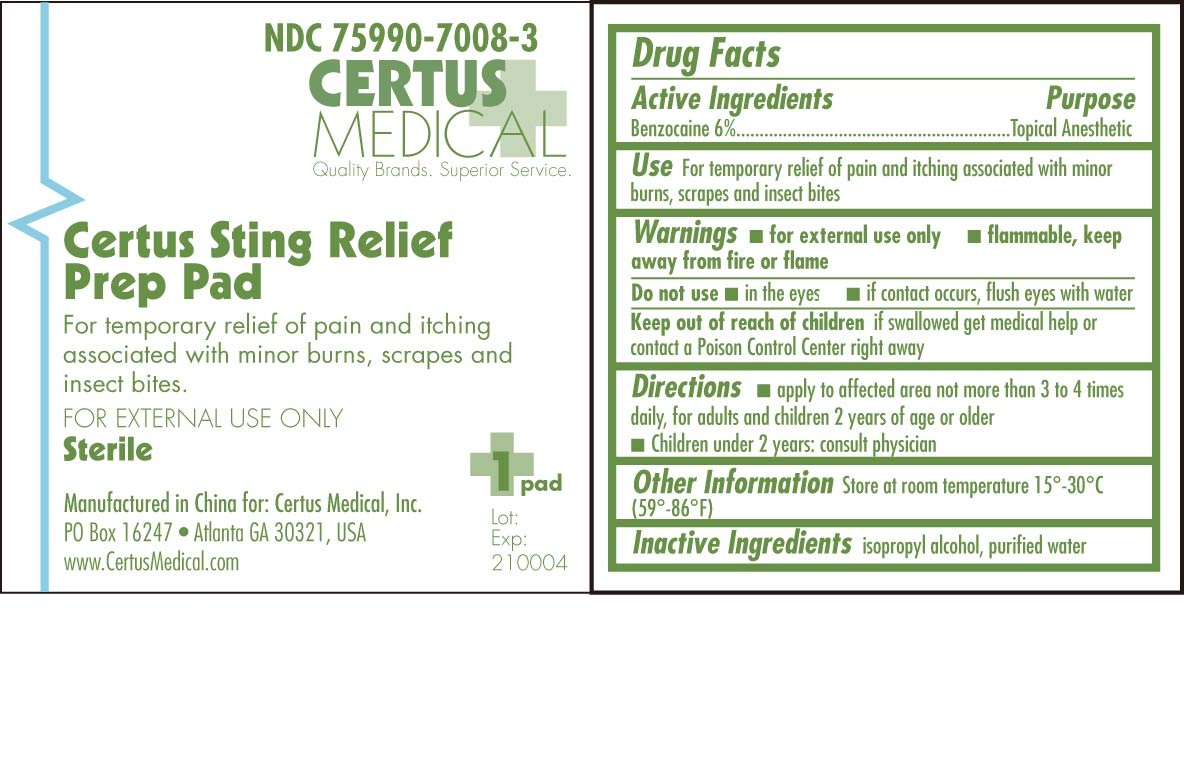 DRUG LABEL: Certus Sting Relief Prep Pad
NDC: 75990-7008 | Form: SWAB
Manufacturer: Certus Medical, Inc.
Category: otc | Type: HUMAN OTC DRUG LABEL
Date: 20110408

ACTIVE INGREDIENTS: BENZOCAINE 0.06 mL/1 mL
INACTIVE INGREDIENTS: WATER; ISOPROPYL ALCOHOL

Certus Sting Relief Prep Pad 210004 Drug Facts and Label

Drug Facts Box OTC Active Ingredient Section

Benzocaine 6%

Drug Facts Box OTC Purpose Section

Topical Anesthetic

Drug Facts Box OTC Indications & Usage Section

For temporary relief of pain and itching associated with minor burns, scrapes and insect bites

Drug Facts Box OTC Warnings Section

for external use only
flammable, keep away from fire or flame

Drug Facts Box OTC Do Not Use Section

in the eyes

if contact occurs, flush eyes with water

Drug Facts Box OTC Keep Out of Reach of Children Section

if swallowed get medical help or contact a Poison Control Center right away

Drug Facts Box OTC Dosage & Administration Section

apply to affected area not more than 3 to 4 times daily, for adults and children 2 years of age or older

children under 2 years: consult physician

Drug Facts Box OTC General Precautions Section

Store at room temperature 15^0 - 30^0 C (59^0 - 86^0 F)

Drug Facts Box OTC Inactive Ingredient Section

isopropyl alcohol, purified water

Certus Sting Relief Prep Pad 210004 pouch

210004.jpg Certus Sting Relief Prep Pad pouch